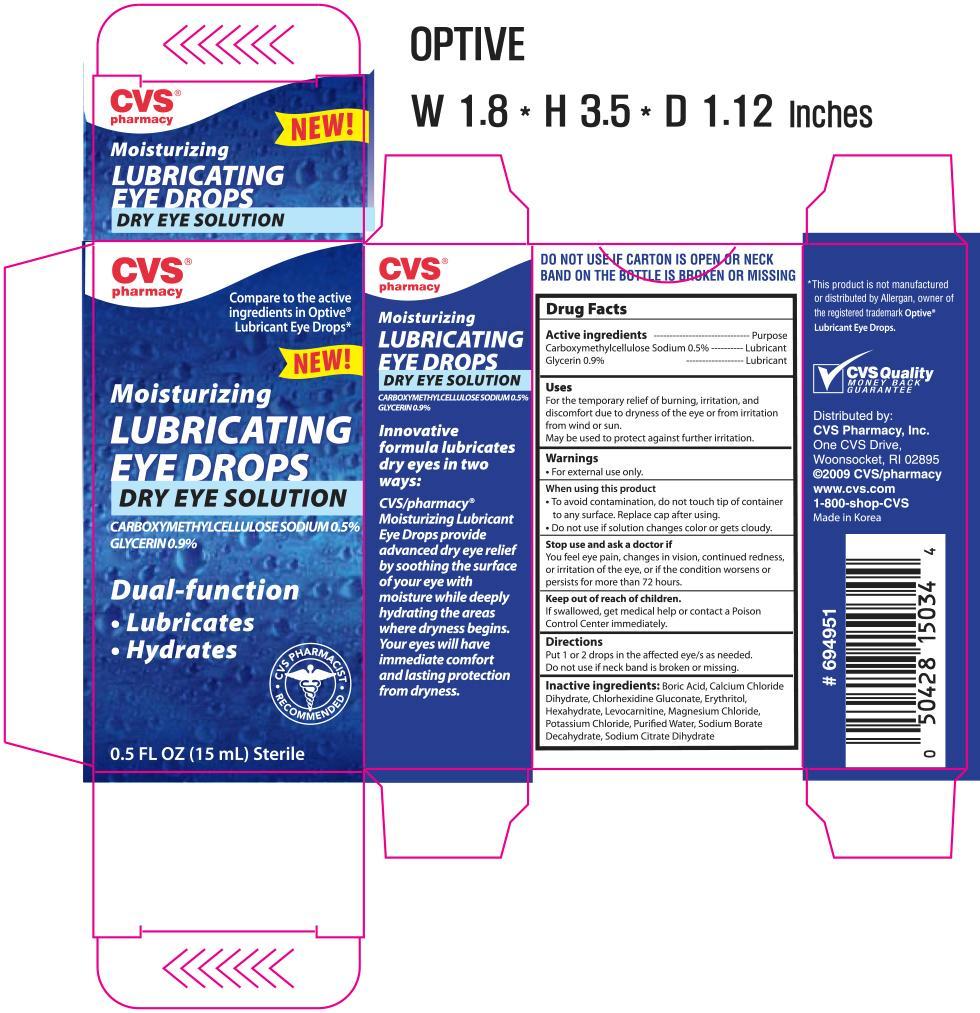 DRUG LABEL: CVS Moisturizing Lubricating Eye
NDC: 59779-150 | Form: SOLUTION/ DROPS
Manufacturer: CVS Pharmacy
Category: otc | Type: HUMAN OTC DRUG LABEL
Date: 20130903

ACTIVE INGREDIENTS: CARBOXYMETHYLCELLULOSE SODIUM 5 mg/100 mg; GLYCERIN 9 mg/100 mg
INACTIVE INGREDIENTS: BORIC ACID; CALCIUM CHLORIDE; CHLORHEXIDINE GLUCONATE; ERYTHRITOL; LEVOCARNITINE; MAGNESIUM CHLORIDE; POTASSIUM CHLORIDE; WATER; SODIUM BORATE; TRISODIUM CITRATE DIHYDRATE

Drug Facts

Active Ingredients Purpose

Carboxymethylcellulose Sodium 0.5% Lubricant

Glycerin 0.9% Lubricant

Uses

For the temporary relief of burning, irritation, and discomfort due to dryness of the eye or from irritation from wind or sun.

May be used to protect against further irritation

Warnings

For external use only.

When using this product

To avoid contamination, do not touch tip of container to any surface. Replace cap after using.

Do not use if solution changes color or gets cloudy.

Stop use and ask a doctor if

You feel eye pain, changes in vision, continued redness, or irritation of the eye, or if the condition worsens or persists for more than 72 hours.

Keep out of reach of children.

If swallowed, get medical help or contact a Poison Control Center immediately.

Directions

Put 1 or 2 drops in the affected eye/s as needed.

Do not use if neck band is broken or missing.

INACTIVE INGREDIENT

Inactive ingredients: Boric Acid, Calcium Chloride Dihydrate, Chlorhexidine Gluconate, Erythritol, Hexahydrate, Levocarnitine, Magnesium Chloride, Potassium Chloride, Purified Water, Sodium Borate Decahydrate, Sodium Citrate Dihydrate

DOSAGE AND ADMINISTRATION

Distributed by:

CVS Pharmacy, Inc.

One CVS Drive,

Woonsocket, RI 02895

Made in Korea